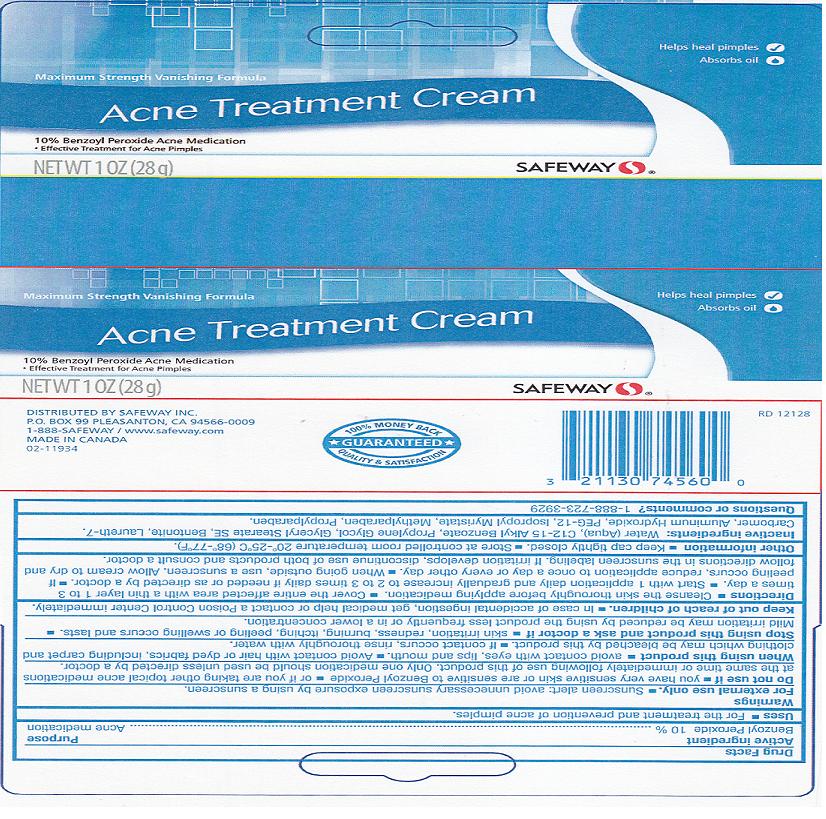 DRUG LABEL: SAFEWAY
NDC: 21130-826 | Form: CREAM
Manufacturer: SAFEWAY INC.
Category: otc | Type: HUMAN OTC DRUG LABEL
Date: 20120611

ACTIVE INGREDIENTS: BENZOYL PEROXIDE 10 g/100 g
INACTIVE INGREDIENTS: WATER; ALKYL (C12-15) BENZOATE; PROPYLENE GLYCOL; GLYCERYL MONOSTEARATE; BENTONITE; LAURETH-7; CARBOMER 934; POTASSIUM HYDROXIDE; ALUMINUM HYDROXIDE; POLYETHYLENE GLYCOL 600; ISOPROPYL MYRISTATE; METHYLPARABEN; PROPYLPARABEN

DRUG FACTS

ACTIVE INGREDIENT

BENZOYL PEROXIDE 10%

PURPOSE

ACNE MEDICATION

USES

FOR THE TREATMENT AND PREVENTION OF ACNE PIMPLES.

WARNINGS

FOR EXTERNAL USE ONLY. SUNSCREEN ALERT: AVOID UNNECESSARY SUNSCREEN EXPOSURE BY USING A SUNSCREEN.

DO NOT USE IF

YOU HAVE VERY SENSITIVE SKIN OR ARE SENSITIVE TO BENZOYL PEROXIDE OR IF YOU ARE TAKING OTHER TOPICAL ACNE MEDICATIONS AT THE SAME OR IMMEDIATELY FOLLOWING USE OF THIS PRODUCT. ONLY ONE MEDICATION SHOULD BE USED UNLESS DIRECTED BY A DOCTOR.

WHEN USING THIS PRODUCT

AVOID CONTACT WITH EYES, LIPS AND MOUTH. AVOID CONTACT WITH HAIR OR DYED FABRICS, INCLUDING CARPET AND CLOTHING WHICH MAY BE BLEACHED BY THIS PRODUCT. IF CONTACT OCCURS, RINSE THOROUGHLY WITH WATER.

STOP USING THIS PRODUCT AND ASK A DOCTOR IF

SKIN IRRITATION, REDNESS, BURNING, ITCHING, PEELING OR SWELLING OCCURS AND LASTS. MILD IRRITATION MAY BE REDUCED BY USING THE PRODUCT LESS FREQUENTLY OR IN A LOWER CONCENTRATION.

KEEP OUT OF REACH OF CHILDREN

IN CASE OF ACCIDENTAL INGESTION, GET MEDICAL HELP OR CONTACT A POISON CONTROL CENTER IMMEDIATELY.

DIRECTIONS

CLEANSE THE SKIN THOROUGHLY BEFORE APPLYING MEDICATION. COVER THE ENTIRE AFFECTED AREA WITH A THIN LAYER 1 TO 3 TIMES A DAY. START WITH 1 APPLICATION DAILY AND GRADUALLY INCREASE TO 2 TO 3 TIMES DAILY IF NEEDED OR AS DIRECTED BY A DOCTOR. IF PEELING OCCURS, REDUCE APPLICATION TO ONCE A DAY OR EVERY OTHER DAY. WHEN GOING OUTSIDE, USE A SUNSCREEN. ALLOW CREAM TO DRY AND FOLLOW DIRECTIONS IN THE SUNSCREEN LABELING. IF IRRITATION DEVELOPS, DISCONTINUE USE OF BOTH PRODUCTS AND CONSULT A DOCTOR.

OTHER INFORMATION

KEEP CAP TIGHTLY CLOSED. STORE AT CONTROLLED ROOM TEMPERATURE 20-25C (68-77F).

INACTIVE INGREDIENTS:

WATER (AQUA), C12-15 ALKYL BENZOATE, PROPYLENE GLYCOL, GLYCERYL STEARATE SE, BENTONITE, LAURETH-7, CARBOMER, ALUMINUM HYDROXIDE, PEG-12, ISOPROPYL MYRISTATE, METHYLPARABEN, PROPYLPARABEN.

QUESTIONS OR COMMENTS?

1-888-723-3929